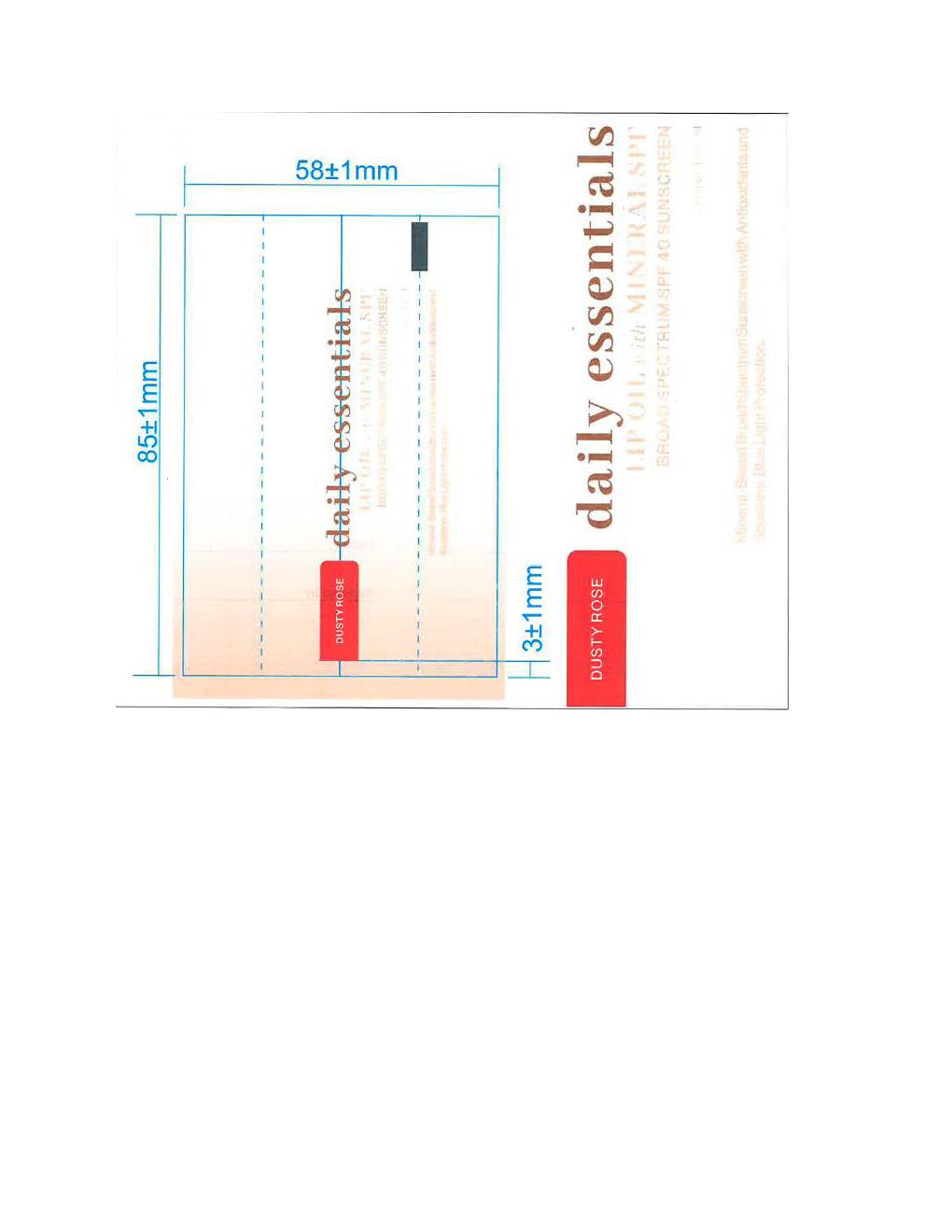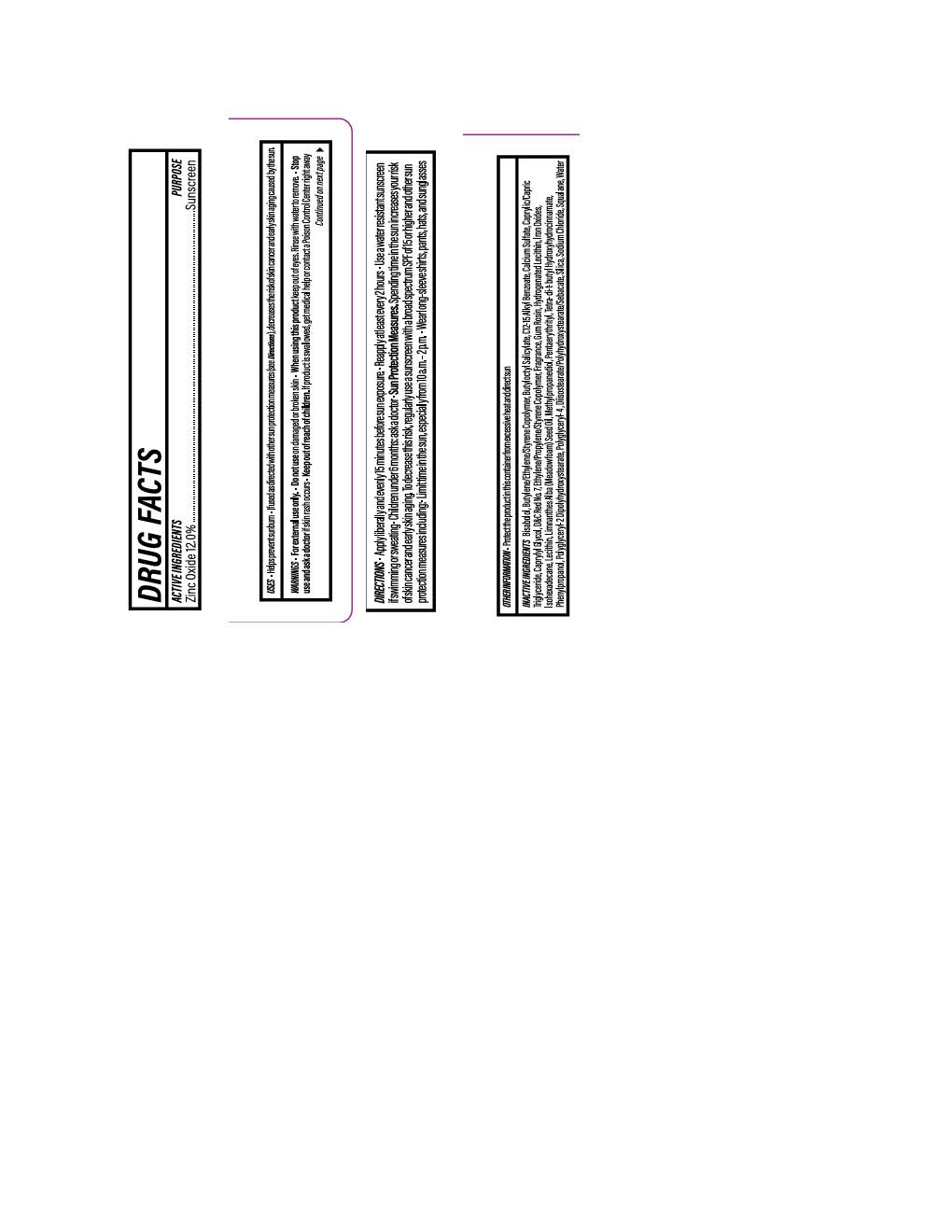 DRUG LABEL: Daily Essential Lip Oil Dusty Rose
NDC: 84891-2181 | Form: LOTION
Manufacturer: Solarium Brands LLC
Category: otc | Type: HUMAN OTC DRUG LABEL
Date: 20251117

ACTIVE INGREDIENTS: ZINC OXIDE 132 mg/1 mL
INACTIVE INGREDIENTS: D&C RED NO. 7; SODIUM CHLORIDE; ISOHEXADECANE; .ALPHA.-BISABOLOL, (+)-; FERRIC OXIDE RED; SILICON DIOXIDE; FERRIC OXIDE YELLOW; FERROSOFERRIC OXIDE; METHYLPROPANEDIOL; LECITHIN, SOYBEAN; SQUALANE; BUTYLOCTYL SALICYLATE; PHENYLPROPANOL; PENTAERYTHRITYL TETRA-DI-T-BUTYL HYDROXYHYDROCINNAMATE; ALKYL (C12-15) BENZOATE; CAPRYLIC/CAPRIC TRIGLYCERIDE; CAPRYLYL GLYCOL; POLYGLYCERYL-4 DIISOSTEARATE/POLYHYDROXYSTEARATE/SEBACATE; LIMNANTHES ALBA (MEADOWFOAM) SEED OIL; WATER; CALCIUM SULFATE

Daily Essential Lip Oil Dusty Rose